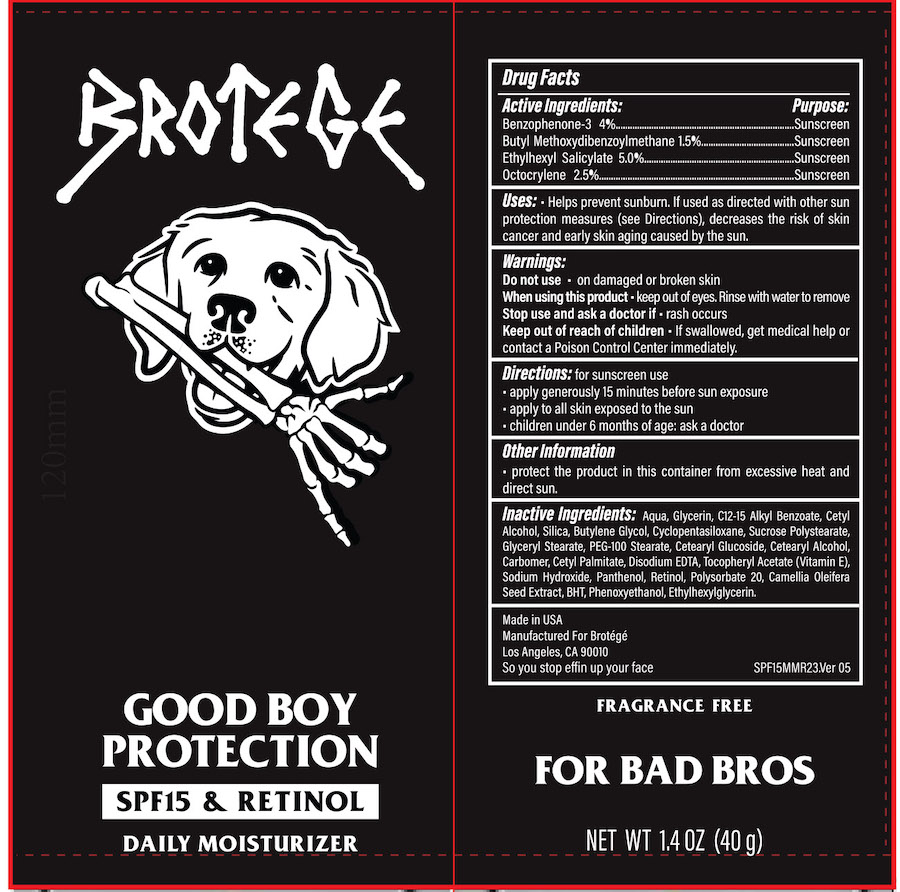 DRUG LABEL: BROTEGE Good Boy Protection SPF 15 and Retinol Daily Moisturizer
NDC: 68062-9981 | Form: CREAM
Manufacturer: Spa de Soleil
Category: otc | Type: HUMAN OTC DRUG LABEL
Date: 20260120

ACTIVE INGREDIENTS: OCTOCRYLENE 1 g/40 mL; OXYBENZONE 0.6 g/40 mL; AVOBENZONE 1.6 g/40 mL; OCTISALATE 2 g/40 mL
INACTIVE INGREDIENTS: CARBOMER 940; WATER; GLYCERIN; C12-15 ALKYL ETHYLHEXANOATE; CETYL ALCOHOL; SILICON DIOXIDE; BUTYLENE GLYCOL; CYCLOMETHICONE; SUCROSE POLYSTEARATE; GLYCERYL STEARATE SE; PEG-100 STEARATE; CETEARYL GLUCOSIDE; CETOSTEARYL ALCOHOL; CETYL PALMITATE; EDETATE DISODIUM; ASCORBYL TOCOPHERYL MALEATE; PANTHENOL; POLYSORBATE 20; CAMELLIA OLEIFERA SEED; BUTYLATED HYDROXYTOLUENE; PHENOXYETHANOL; ETHYLHEXYLGLYCERIN; RETINOL; SODIUM HYDROXIDE

Moisturizer Sunscreen SPF 50

Active Ingredients

Benzophenone-3 4%

Butyl Methoxydibenzoylmethane 1.5%

Ethylhexyl Salicylate 5.0%

Octocrylene 2.5%

Purpose

Sunscreen

Warnings

Do not use on damaged or broken skin

When using this product

- keep out of the eye area
- rinse with water to remove
- stop use and ask a doctor if rash or irritation develops
- for external use onlyl
- keep out of reach of children

KEEP OUT OF REACH OF CHILDREN

Directions

Directions: for sunscreen use

• apply generously 15 minutes before sun exposure

• apply to all skin exposed to the sun

• children under 6 months of age: ask a doctor

INDICATIONS AND USAGE

Apply generously and evenly thirty minutes before sun exposure. Reapply at least every two hours.

Inactive Ingredients

Inactive Ingredients: Aqua, Glycerin, C12-15 Alkyl Benzoate, Cetyl Alcohol, Silica, Butylene Glycol, Cyclopentasiloxane, Sucrose Polystearate, Glyceryl Stearate, PEG-100 Stearate, Cetearyl Glucoside, Cetearyl Alcohol, Carbomer, Cetyl Palmitate, Disodium EDTA, Tocopheryl Acetate (Vitamin E), Sodium Hydroxide, Panthenol, Retinol, Polysorbate 20, Camellia Oleifera Seed Extract, BHT, Phenoxyethanol, Ethylhexylglycerin